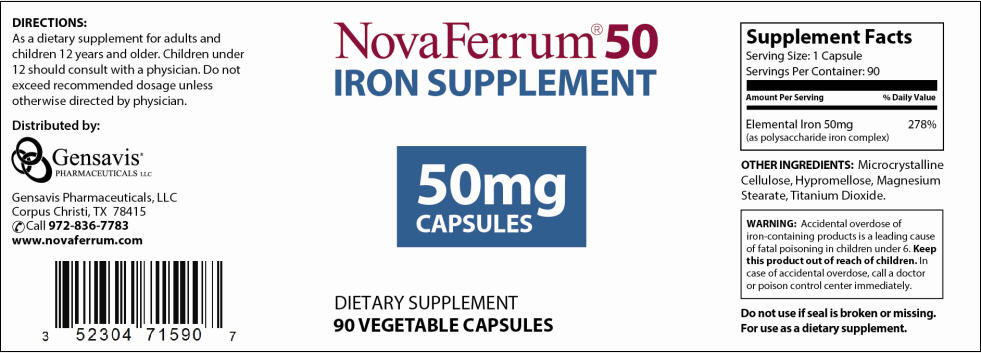 DRUG LABEL: NovaFerrum 
NDC: 52304-715 | Form: CAPSULE
Manufacturer: Gensavis Pharmaceuticals, LLC
Category: other | Type: DIETARY SUPPLEMENT
Date: 20131031

ACTIVE INGREDIENTS: iron 50 mg/1 1
INACTIVE INGREDIENTS: CELLULOSE, MICROCRYSTALLINE; HYPROMELLOSES; MAGNESIUM STEARATE; TITANIUM DIOXIDE

NovaFerrum 50
Iron Supplement

STATEMENT OF IDENTITY

Supplement Facts

Serving Size: 1 capsule
Servings Per Container: 90

Amount Per Serving | % Daily Value
Elemental Iron 50mg (as polysaccharide iron complex) | 278%

HEALTH CLAIM

OTHER INGREDIENTS: Microcrystalline Cellulose, Hypromellose, Magnesium Stearate, Titanium Dioxide.

WARNING

Accidental overdose of iron-containing products is a leading cause of fatal poisoning in children under 6. Keep this product out of reach of children. In case of accidental overdose, call a doctor or poison control center immediately.

Do not use if seal is broken or missing.

For use as a dietary supplement.

Suggested use

As a dietary supplement take one capsule daily or as directed by a physician. For adults and children 12 years and older. Do not exceed recommended dosage unless otherwise directed by a physician.

WARNINGS

WARNING: If you are pregnant or lactating, consult your physician before using this product.

HEALTH CLAIM

Distributed by:
Gensavis Pharmaceuticals, LLC
Corpus Christi, TX 78415
Call 972-836-7783
www.novaferrum.com

PRINCIPAL DISPLAY PANEL - 50mg Capsule Bottle Label

NovaFerrum® 50
IRON SUPPLEMENT

50mg
CAPSULES

DIETARY SUPPLEMENT
90 VEGETABLE CAPSULES